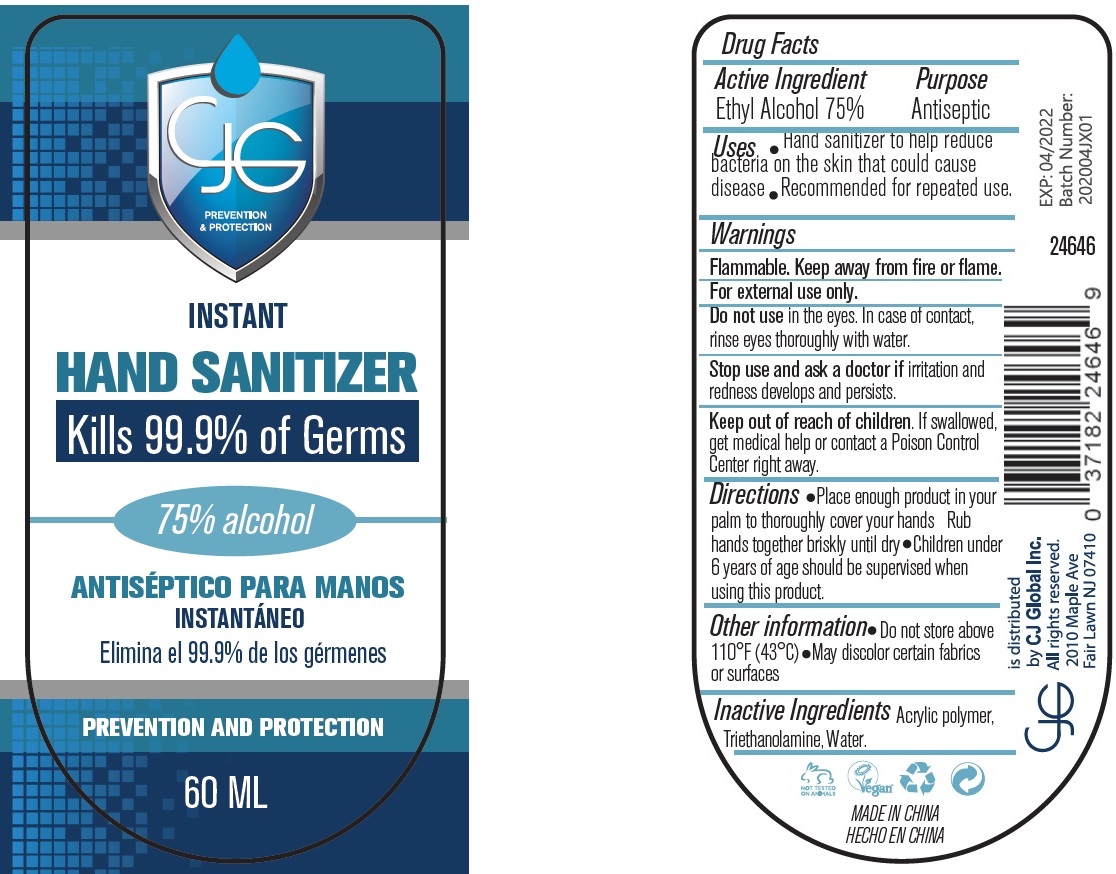 DRUG LABEL: Instant Hand Sanitizer
NDC: 77372-000 | Form: LIQUID
Manufacturer: CJ Global INC
Category: otc | Type: HUMAN OTC DRUG LABEL
Date: 20200817

ACTIVE INGREDIENTS: ALCOHOL 0.75 mL/1 mL
INACTIVE INGREDIENTS: CARBOMER INTERPOLYMER TYPE A (55000 CPS); TROLAMINE; WATER

Instant Hand Sanitizer

Active Ingredient

Ethyl Alcohol 75%

Purpose

Antiseptic

Uses

- Hand sanitizer to help reduce bacteria on the skin that could cause disease
- Recommended for repeated use.

Warnings

Flammable. Keep away from fire or flame.
For external use only.

Do not use

in the eyes. In case of contact, rinse eyes thoroughly with water.

Stop use and ask a doctor if

irritation and redness develops and persists.

Keep out of reach of children.

If swallowed, get medical help or contact a Poison Control Center right away.

Directions

- Place enough product in your palm to thoroughly cover your hands Rub hands together briskly until dry
- Children under 6 years of age should be supervised when using this product.

Other information

- Do not store above 110°F (43°C)
- May discolor certain fabrics or surfaces

Inactive Ingredients

Acrylic polymer, Triethanolamine, Water.